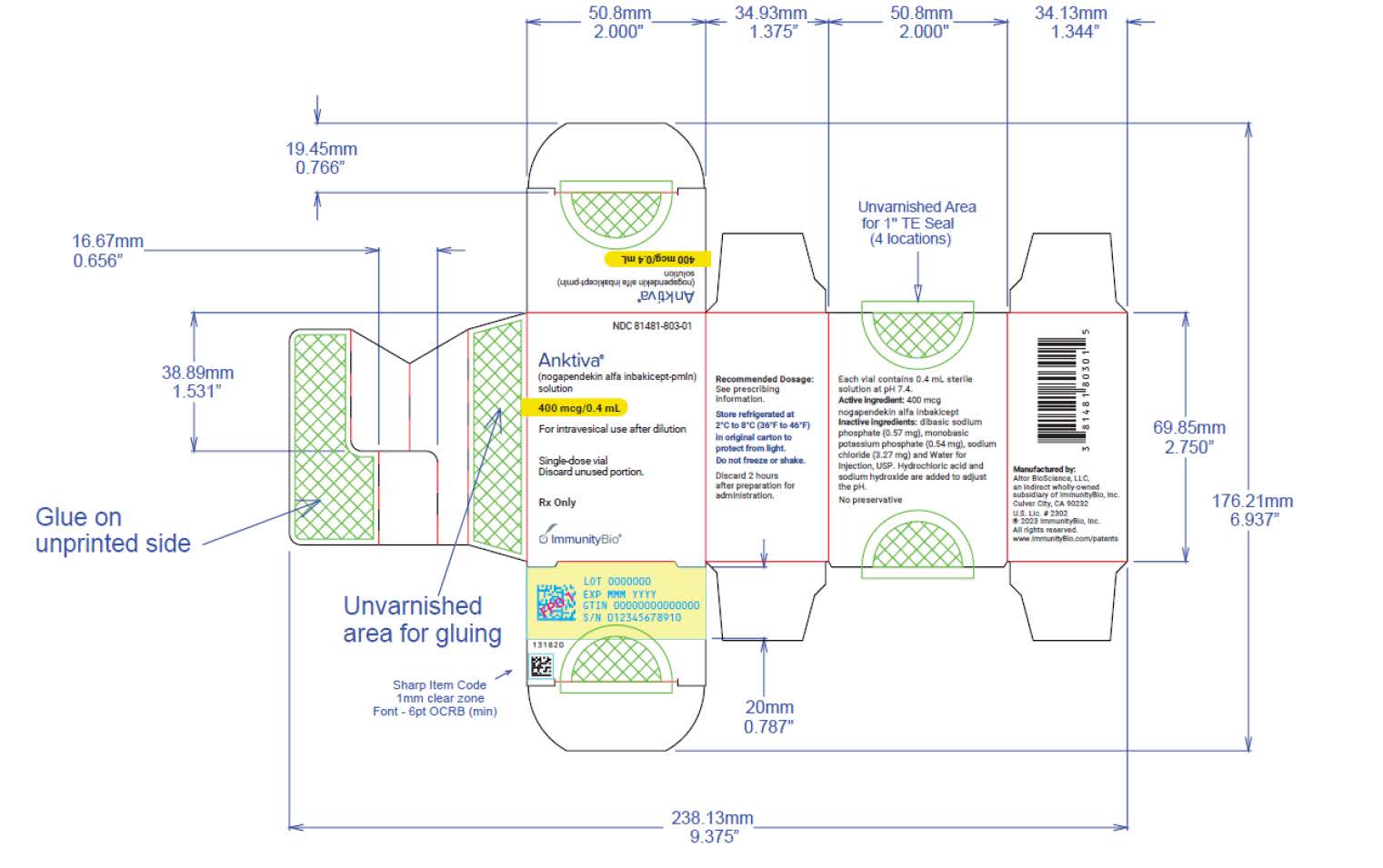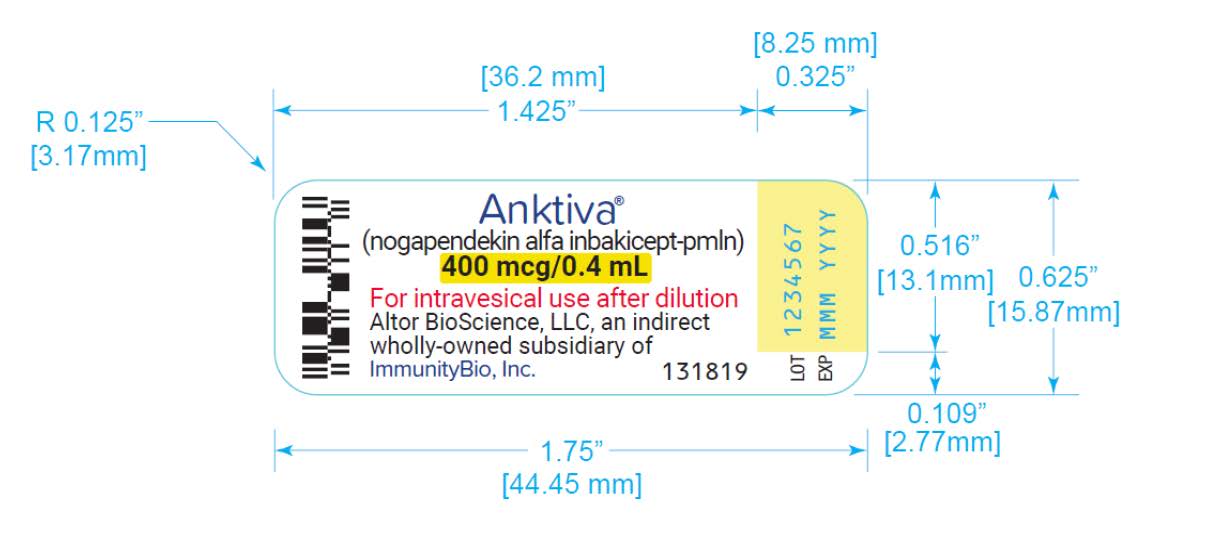 DRUG LABEL: ANKTIVA
NDC: 81481-803 | Form: SOLUTION
Manufacturer: Altor BioScience, LLC, an indirect wholly-owned subsidiary of ImmunityBio, Inc.
Category: prescription | Type: HUMAN PRESCRIPTION DRUG LABEL
Date: 20250624

ACTIVE INGREDIENTS: NOGAPENDEKIN ALFA INBAKICEPT-PMLN 400 ug/0.4 mL
INACTIVE INGREDIENTS: SODIUM PHOSPHATE, DIBASIC, ANHYDROUS 0.57 mg/0.4 mL; SODIUM CHLORIDE 3.27 mg/0.4 mL; MONOBASIC POTASSIUM PHOSPHATE 0.54 mg/0.4 mL

HIGHLIGHTS OF PRESCRIBING INFORMATION

These highlights do not include all the information needed to use ANKTIVA safely and effectively. See full prescribing information for ANKTIVA.
ANKTIVA® (nogapendekin alfa inbakicept-pmln) solution, for intravesical use
Initial U.S. Approval: 2024

1 INDICATIONS AND USAGE

ANKTIVA is an interleukin-15 (IL-15) receptor agonist indicated with Bacillus Calmette-Guérin (BCG) for the treatment of adult patients with BCG-unresponsive nonmuscle invasive bladder cancer (NMIBC) with carcinoma in situ (CIS) with or without papillary tumors. (1)

2 DOSAGE AND ADMINISTRATION

For Intravesical Use Only

- For induction: 400 mcg administered intravesically with BCG once a week for 6 weeks. A second induction course may be administered if complete response is not achieved at month 3. (2.1)
- For maintenance: 400 mcg administered intravesically with BCG once a week for 3 weeks at months 4, 7, 10, 13 and 19. For patients with an ongoing complete response at month 25 and later, additional maintenance instillations with BCG may be administered once a week for 3 weeks at months 25, 31, and 37. (2.1)
- Instill intravesically only after dilution. Total time from vial puncture to the completion of the intravesical instillation should not exceed 2 hours. (2.2)

See full Prescribing Information for dilution and administration instructions.

3 DOSAGE FORMS AND STRENGTHS

400 mcg/0.4 mL, clear to slightly opalescent and colorless to slightly yellow solution in single-dose vials for intravesical instillation after dilution. (3)

4 CONTRAINDICATIONS

None (4)

5 WARNINGS AND PRECAUTIONS

- Delaying cystectomy can lead to the development of metastatic bladder cancer, which can be lethal. (5.1)

6 ADVERSE REACTIONS

The most common (≥15%) adverse reactions, including laboratory test abnormalities, are increased creatinine, dysuria, hematuria, urinary frequency, micturition urgency, urinary tract infection, increased potassium, musculoskeletal pain, chills and pyrexia. (6.1)

To report SUSPECTED ADVERSE REACTIONS, contact Altor BioScience, LLC, an indirect wholly-owned subsidiary of ImmunityBio, Inc. at toll-free phone 877-265-8482 or FDA at 1-800-FDA-1088 or www.fda.gov/medwatch.

8 USE IN SPECIFIC POPULATIONS

- Pregnancy: May cause fetal harm. Advise females of reproductive potential of the potential risk to a fetus and to use effective contraception. (8.1, 8.3)

FULL PRESCRIBING INFORMATION

1 INDICATIONS AND USAGE

ANKTIVA in combination with Bacillus Calmette-Guérin (BCG) is indicated for the treatment of adult patients with BCG-unresponsive nonmuscle invasive bladder cancer (NMIBC) with carcinoma in situ (CIS) with or without papillary tumors.

2 DOSAGE AND ADMINISTRATION

2.1 Recommended Dosage

For Intravesical Use Only. Do NOT administer by subcutaneous or intravenous or intramuscular routes.

- For induction: ANKTIVA is recommended at a dose of 400 mcg administered intravesically with BCG once a week for 6 weeks. A second induction course may be administered if complete response is not achieved at month 3.
- For maintenance: After BCG and ANKTIVA induction therapy, ANKTIVA is recommended at a dose of 400 mcg administered intravesically with BCG once a week for 3 weeks at months 4, 7, 10, 13 and 19 (for a total of 15 doses). For patients with an ongoing complete response at month 25 and later, maintenance instillations with BCG may be administered once a week for 3 weeks at months 25, 31, and 37 for a maximum of 9 additional instillations.

The recommended duration of treatment is until disease persistence after second induction, disease recurrence or progression, unacceptable toxicity, or a maximum of 37 months.

2.2 Preparation and Administration

Preparation of Agent
See BCG Prescribing Information for information on preparation and handling of BCG.

Parenteral drug products should be inspected visually for particulate matter and discoloration prior to administration, whenever solution and container permit. The solution is clear to slightly opalescent and colorless to slightly yellow. Discard the vial if visible particles are observed.

Draw 0.4 mL of ANKTIVA into a small syringe and using aseptic technique add to the saline containing the BCG suspension that has been prepared following the instructions provided in the Prescribing Information for BCG. Mix the suspension gently. Using a 60-mL syringe connected to an appropriate size needle, withdraw the ANKTIVA BCG mixture to a final volume of 50 mL.

If the admixture of ANKTIVA in combination with BCG is not used immediately, store refrigerated at 2°C to 8°C (36°F to 46°F) and use within 2 hours. Unused solution of admixture should be discarded after 2 hours.

Treatment
The admixture of ANKTIVA in combination with BCG is instilled into the bladder via a catheter. After instillation is complete, the catheter is removed. The ANKTIVA in combination with BCG admixture is retained in the bladder for 2 hours and then voided. Patients unable to retain the suspension for 2 hours should be allowed to void sooner, if necessary. Do not repeat the dose if the patient voids before 2 hours.

See BCG Prescribing Information for information on retention in the bladder and patient positioning during bladder instillation.

3 DOSAGE FORMS AND STRENGTHS

400 mcg/0.4 mL, clear to slightly opalescent and colorless to slightly yellow solution in single-dose vials for intravesical instillation after dilution.

4 CONTRAINDICATIONS

None

5 WARNINGS AND PRECAUTIONS

5.1 Risk of Metastatic Bladder Cancer with Delayed Cystectomy

Delaying cystectomy in patients with BCG-unresponsive CIS could lead to development of muscle invasive or metastatic bladder cancer, which can be lethal. The risk of developing muscle invasive or metastatic bladder cancer increases the longer cystectomy is delayed in the presence of persisting CIS.

Of the 77 evaluable patients with BCG-unresponsive CIS treated with ANKTIVA with BCG in QUILT-3.032, 10% (n = 8) progressed to muscle invasive (T2 or greater) bladder cancer, including 7 during the treatment period. Three patients had progression determined at the time of cystectomy. The median time between determination of persistent or recurrent CIS and progression to muscle-invasive disease was 107 days (range: 0 – 210).

If patients with CIS do not have a complete response to treatment after a second induction course of ANKTIVA with BCG, reconsider cystectomy.

6 ADVERSE REACTIONS

6.1 Clinical Trials Experience

Because clinical trials are conducted under widely varying conditions, adverse reaction rates observed in the clinical trials of a drug cannot be directly compared to rates in the clinical trials of another drug and may not reflect the rates observed in practice.

The safety of ANKTIVA with BCG was evaluated in Cohort A of QUILT-3.032, a single-arm, multicenter clinical study in 88 patients with BCG-unresponsive high-grade NMIBC with CIS with or without Ta/T1 papillary disease [see Clinical Studies (14)]. Patients received 400 mcg ANKTIVA with BCG weekly for 6 consecutive weeks during induction and then once a week for every 3 weeks at 4, 7, 10, 13, and 19 months for patients with no or low grade disease. Patients with persistent CIS or high grade Ta at 3 months were eligible to receive a second induction. Patients with ongoing CR at 25 months were eligible to receive additional instillations once a week every 3 weeks at months 25, 31, and 37. The median number of doses of ANKTIVA with BCG administered to patients was 12 (range 2 – 30) doses. The median duration of exposure to ANKTIVA with BCG was 7.1 months (range: 0.26 to 36.3 months).

Serious adverse reactions occurred in 16% of patients receiving ANKTIVA with BCG. Serious adverse reactions that occurred in ≥2% of patients who received ANKTIVA with BCG included hematuria (3.4%). A fatal adverse reaction of cardiac arrest occurred in 1 (1.1%) patient receiving ANKTIVA with BCG.

Permanent discontinuation of ANKTIVA with BCG due to adverse reactions occurred in 7% of patients. Adverse reactions (>2%) resulting in permanent discontinuation of ANKTIVA with BCG included musculoskeletal pain (2.3%).

Dosage interruptions due to adverse reactions occurred in 34% of patients receiving ANKTIVA with BCG. Adverse reactions (≥5%) that resulted in interruption of ANKTIVA with BCG were urinary tract infection (10%), dysuria (8%), hematuria (6%), and bladder irritation (6%).

Dosage reductions due to adverse reactions were not permitted for ANKTIVA; however, dose reduction of BCG was allowed for adverse reactions and occurred in 3.4% of patients including (>1%) urinary tract infection (2.3%), hematuria (1.1%), urinary frequency (1.1%), and bladder irritation (1.1%).

The most common (≥15%) adverse reactions, including laboratory test abnormalities, were increased creatinine, dysuria, hematuria, urinary frequency, micturition urgency, urinary tract infection, increased potassium, musculoskeletal pain, chills and pyrexia.

Table 1 summarizes the adverse reactions in Cohort A of QUILT-3.032.

Table 1: Adverse Reactions Occurring in ≥15% of Patients in Cohort A in QUILT-3.032
Adverse Reaction | ANKTIVA with BCG (n=88)
Adverse Reaction | All Grades % | Grades 3 or 4 %
Dysuria | 32 | 0
Hematuria^1 | 32 | 3.4
Urinary Frequency | 27 | 0
Micturition Urgency^1 | 25 | 0
Urinary Tract Infection^1 | 24 | 2.3
Musculoskeletal Pain^1 | 17 | 2.3
Chills | 15 | 0
Pyrexia | 15 | 0
^1Includes other related terms

Clinically relevant adverse reactions in <15% of patients who received ANKTIVA with BCG included fatigue (14%), nausea (14%), bladder irritation (11%), diarrhea (9%), and nocturia (7%).

Table 2 summarizes the laboratory test abnormalities occuring in ≥15% of patients in QUILT-3.032.

Table 2: Select Laboratory Test Abnormalities (≥15%) That Worsened From Baseline in Patients in Cohort A of QUILT-3.032
Laboratory Abnormality | ANKTIVA with BCG^1 (n=88)
Laboratory Abnormality | All Grades % | Grades 3 or 4 %
Increased Creatinine | 76 | 0
Increased Potassium | 18 | 2
^1The denominator used to calculate the rates was 88 based on the number of patients with a baseline value and at least one post-treatment value.

8 USE IN SPECIFIC POPULATIONS

8.1 Pregnancy

Risk Summary
Systemic exposure of nogapendekin alfa inbakicept-pmln following intravesical administration of the approved dosage of ANKTIVA was below the limit of quantitation [see Clinical Pharmacology 12.3)] .

Based on its mechanism of action, ANKTIVA may cause fetal harm when administered to a pregnant woman if systemic exposure occurs [see Clinical Pharmacology (12.1)] . There are no available data on ANKTIVA use in pregnant women to inform a drug-associated risk. Animal reproductive and developmental toxicity studies have not been conducted with nogapendekin alfa inbakicept-pmln. Advise pregnant women and females of reproductive potential of the potential risk to a fetus.

The estimated background risk of major birth defects and miscarriage for the indicated population is unknown. In the U.S. general population, the estimated background risk of major birth defects and miscarriage in clinically recognized pregnancies is 2-4% and 15-20%, respectively.

8.2 Lactation

Risk Summary
There are no data on the presence of nogapendekin alfa inbakicept-pmln in human milk, or the effects on the breastfed child, or on milk production. Systemic exposure of nogapendekin alfa inbakicept-pmln in patients receiving intravesical administration of the approved dosage of ANKTIVA was below the limit of quantitation [see Clinical Pharmacology (12.3)] , indicating any amount in the milk will be low. The developmental and health benefits of breastfeeding should be considered along with the mother’s clinical need for ANKTIVA and any potential adverse effects on the breastfed child from ANKTIVA or from the underlying maternal condition.

8.3 Females and Males of Reproductive Potential

Based on its mechanism of action, ANKTIVA may cause fetal harm when administered to a pregnant woman [see Use in Specific Populations (8.1)] .

Pregnancy Testing
Verify pregnancy status in females of reproductive potential prior to initiating treatment with ANKTIVA.

Contraception
Advise females of reproductive potential to use effective contraception during treatment with ANKTIVA and for 1 week after the last dose.

8.4 Pediatric Use

Safety and effectiveness of ANKTIVA in pediatric patients have not been established.

8.5 Geriatric Use

Of the total number of patients in clinical studies of ANKTIVA for BCG-unresponsive NMIBC, 84% were 65 years of age or older and 40% were 75 years or older. Clinical studies of ANKTIVA did not include sufficient numbers of younger adult patients to determine if patients 65 years of age and older respond differently than younger adult patients.

11 DESCRIPTION

Nogapendekin alfa inbakicept-pmln is an interleukin-15 (IL-15) receptor agonist. It is a soluble complex consisting of (a) nogapendekin alfa (a human IL-15N72D variant, 114 amino acids) bound to (b) inbakicept [a dimeric human IL-15Rα sushi domain (65 amino acids)/human IgG1 Fc fusion protein (232 amino acids)]. Each fully assembled nogapendekin alfa inbakicept-pmln complex consists of a single inbakicept and two nogapendekin alfa components. Each IL-15N72D component is bound to one of the IL-15Rα sushi domains.

The recombinant protein complex is produced by a recombinant cell line that was created by transfecting a Chinese hamster ovary (CHO-K1) cell line with plasmids carrying genes for the IL-15N72D and IL-15RαSu/IgG1 Fc proteins. Purification of the product is achieved by conventional chromatography. The molecular weight of the deglycosylated nogapendekin alfa inbakicept-pmln complex is 92,106.5 Da. The molecular weights of the individual deglycosylated sub-units are 66565.6 Da (dimer) and 12,770.45 Da for the IL-15RαSu/IgG1 Fc domain and the IL-15N72D domain, respectively.

ANKTIVA (nogapendekin alfa inbakicept-pmln) solution is a clear to slightly opalescent, colorless to slightly yellow solution provided in a single-dose vial containing 400 mcg in 0.4 mL for intravesical administration upon dilution [see Dosage and Administration (2)] . Each vial also contains dibasic sodium phosphate (0.57 mg), monobasic potassium phosphate (0.54 mg), sodium chloride (3.27 mg) and Water for Injection, USP. Hydrochloric acid and sodium hydroxide is added to adjust the pH to 7.4.

12 CLINICAL PHARMACOLOGY

12.1 Mechanism of Action

Nogapendekin alfa inbakicept-pmln is an IL-15 receptor agonist. IL-15 signals through a heterotrimeric receptor that is composed of the common gamma chain (γc) subunit, the beta chain (βc) subunit, and the IL-15-specific alpha subunit, IL-15 receptor α. IL-15 is trans-presented by the IL-15 receptor α to the shared IL-2/IL-15 receptor (βc and γc) on the surface of CD4^+and CD8^+T cells and NK cells.

Binding of nogapendekin alfa inbakicept-pmln to its receptor results in proliferation and activation of NK, CD8^+, and memory T cells without proliferation of immuno-suppressive Treg cells. In vivo, intravesicular nogapendekin alfa inbakicept-pmln alone or in combination with BCG showed anti-tumor activity when compared to BCG alone, in a carcinogen-induced model of bladder cancer in immunocompetent rats.

12.2 Pharmacodynamics

The exposure-response relationship and time course of pharmacodynamic response for the safety and effectiveness of nogapendekin alfa inbakicept-pmln have not been fully characterized.

12.3 Pharmacokinetics

Systemic exposure of nogapendekin alfa inbakicept-pmln was less than 100 pg/mL following the approved recommended dosage in all patients. This was below the lower limit of quantitation in all patients.

12.6 Immunogenicity

There is insufficient information to characterize the anti-drug antibody response to ANKTIVA and the effects of anti-drug antibodies on pharmacokinetics, pharmacodynamics, safety, or effectiveness of nogapendekin alfa inbakicept-pmln products.

13 NONCLINICAL TOXICOLOGY

13.1 Carcinogenesis, Mutagenesis, Impairment of Fertility

Carcinogenicity and genotoxicity studies have not been conducted with nogapendekin alfa inbakicept-pmln.

Fertility studies with nogapendekin alfa inbakicept-pmln have not been conducted.

14 CLINICAL STUDIES

The efficacy of ANKTIVA was evaluated in QUILT-3.032 (NCT03022825), a single-arm, multicenter trial in 77 adults with BCG-unresponsive, high-risk, NMIBC with CIS with or without Ta/T1 papillary disease following transurethral resection.

BCG unresponsive high-risk NMIBC CIS was defined as persistent or recurrent CIS alone or with Ta/T1 disease within 12 months of completion of adequate BCG therapy. Adequate BCG therapy was defined as administration of at least 5 of 6 doses of an initial induction course plus either of at least 2 of 3 doses of maintenance therapy or at least 2 of 6 doses of a second induction course. Prior to treatment, all patients with Ta or T1 disease had undergone transurethral resection of bladder tumor (TURBT) to remove all resectable disease. Residual CIS not amenable to complete resection, fulguration, or cauterization was permitted. The trial excluded patients with history of or evidence of muscle invasive (i.e., T2, T3, T4), locally advanced, metastatic, and/or extra-vesical (i.e., urethra, ureter, or renal pelvis) bladder cancer.

Patients received 400 mcg ANKTIVA with BCG weekly for 6 consecutive weeks during the induction treatment period and then once a week every 3 weeks at 4, 7, 10, 13, and 19 months for patients with no or low grade disease. Patients with persistent CIS or high grade Ta disease at 3 months were eligible to receive a second induction course. Patients with ongoing CR at 25 months were eligible to receive additional instillations once a week every 3 weeks at months 25, 31, and 37. Assessment of tumor status was performed every 3 months for up to two years. Assessment for ongoing response beyond month 24 was per local community standards. Random or cystoscopy directed biopsies were required within the first 6 months after treatment initiation. The major efficacy outcome measures were complete response (CR) at any time (as defined by negative results for cystoscopy [with TURBT/biopsies as applicable] and urine cytology) and duration of response.

The median age of patients was 73 years (range, 50–91 years); 86% were male; race was White (90%), Black (6%), Asian (1%), American Indian or Alaska Native (1%), or Unknown (1%); and patients had baseline ECOG performance status of 0 (83%) or 1 (17%).

Tumor characteristics at study entry were CIS without Ta/T1 papillary disease (69%), CIS with Ta papillary disease (21%) or CIS with T1 +/- Ta papillary disease (10%). Baseline high-risk NMIBC disease status was 43% refractory and 57% relapsed. The median number of prior BCG doses received was 12 doses (range: 8–45 doses); 13% received partial-dose prior BCG. Baseline cystoscopy imaging modality was white light (57%), blue light or narrow band imaging (40%), and unknown (3%).

Efficacy results are summarized in Table 3. Thirty-one percent (n=24) of patients received a second induction course.

Table 3: Efficacy Results in QUILT-3.032
 | ANKTIVA with BCG (n=77)
Complete Response Rate (95% CI) | 62% (51, 73)
Duration of Responsea
Range in months | 0.0, 47.0+
% (n) with duration ≥ 12 months | 58% (28)
% (n) with duration ≥ 24 months | 40% (19)
+ Denotes ongoing response
aBased on 48 patients that achieved a complete response at any time; reflects period from the time complete response was achieved.

16 HOW SUPPLIED/STORAGE AND HANDLING

ANKTIVA (nogapendekin alfa inbakicept-pmln) is clear to slightly opalescent and colorless to slightly yellow solution available in:

Carton containing 400 mcg/0.4 mL, single-dose vial (NDC 81481-803-01).

Store vials under refrigeration at 2°C to 8°C (36°F to 46°F) in the original carton to protect from light. Do not freeze. Do not shake.

17 PATIENT COUNSELING INFORMATION

Risk of Metastatic Bladder Cancer with Delayed Cystectomy

- Inform patients that delaying cystectomy could lead to development of metastatic bladder cancer. Discuss the risk of metastatic bladder cancer and that the risk increases the longer cystectomy is delayed in the presence of persisting CIS [see Warnings and Precautions (5.1)].

Local Adverse Reactions Before and During Treatment

- Inform patients that irritable bladder symptoms may occur during instillation, and retention of ANKTIVA, and following voiding [see Adverse Reactions (6.1)].
- Inform patients that for the first 24 hours following administration, red-tinged urine may occur.
- Advise patients to immediately report prolonged irritable bladder symptoms or prolonged passage of red-colored urine to their healthcare provider.
- Instruct patients to maintain adequate hydration following ANKTIVA treatment.

Administration

- Inform patients that the ANKTIVA in combination with BCG admixture should be retained in the bladder for 2 hours and then voided.
- Advise patients that if unable to retain the suspension for 2 hours they can void sooner if necessary [see Dosage and Administration (2.2)]
- Instruct patients to void while seated to avoid splashing of urine.

Embryo-Fetal Toxicity

- Advise pregnant women and females of reproductive potential of the potential risk to a fetus. Advise females to inform their healthcare provider of a known or suspected pregnancy [see Use in Specific Populations (8.1)] .
- Advise females of reproductive potential to use effective contraception during treatment with ANKTIVA and for 1 week after the last dose [see Use in Specific Populations (8.3)] .

See the BCG prescribing information, Information for Patients for additional patient counseling information.

Manufactured for: Altor BioScience, LLC, an indirect wholly-owned subsidiary of ImmunityBio, Inc., Culver City, CA 90232 Manufactured by AGC Biologics, 21511 23rdDr. SE, Bothell, WA 98021
U.S. license number 2302

ANKTIVA Label
NDC: 81481–803–01

ANKTIVA Box
NDC: 81481–803–01